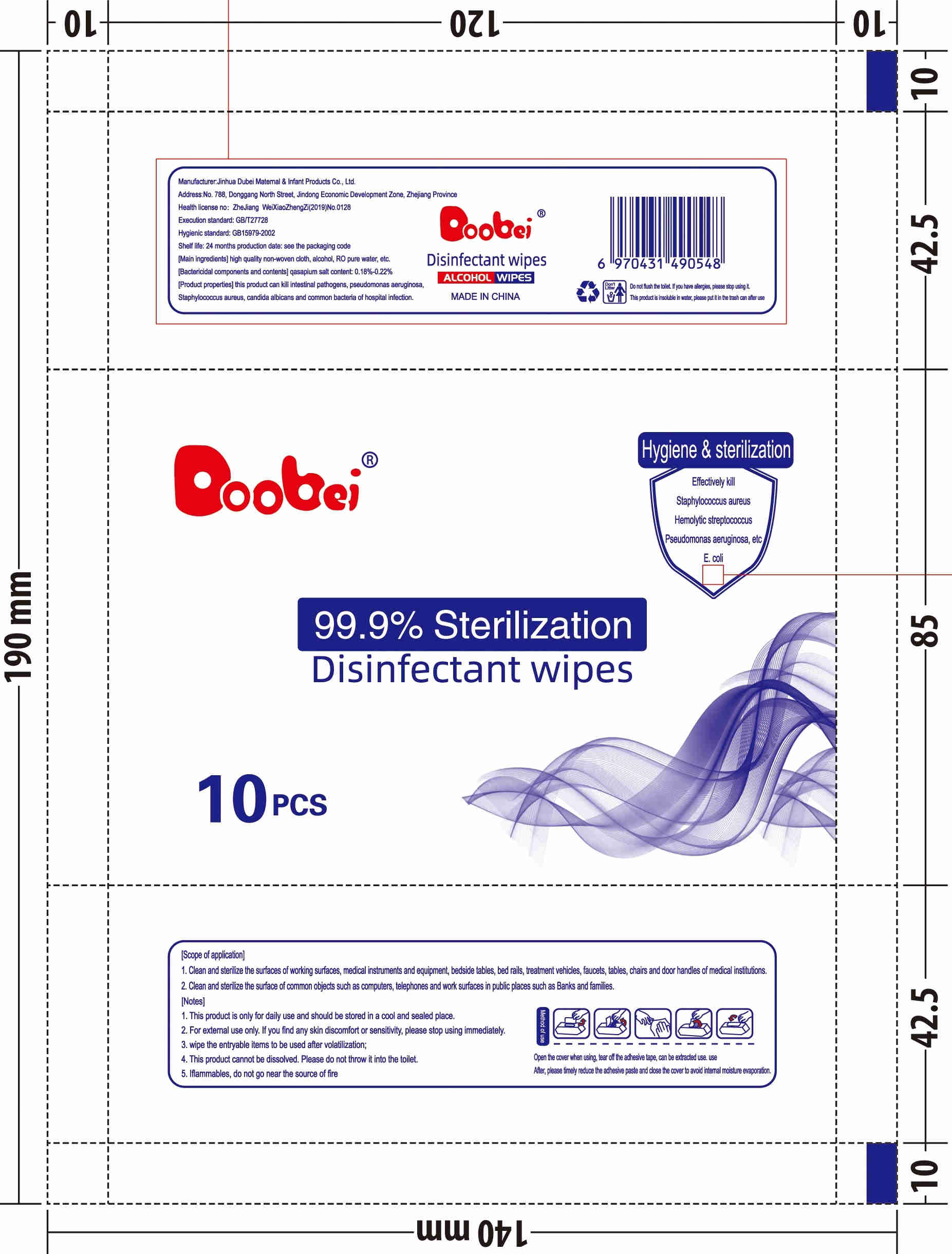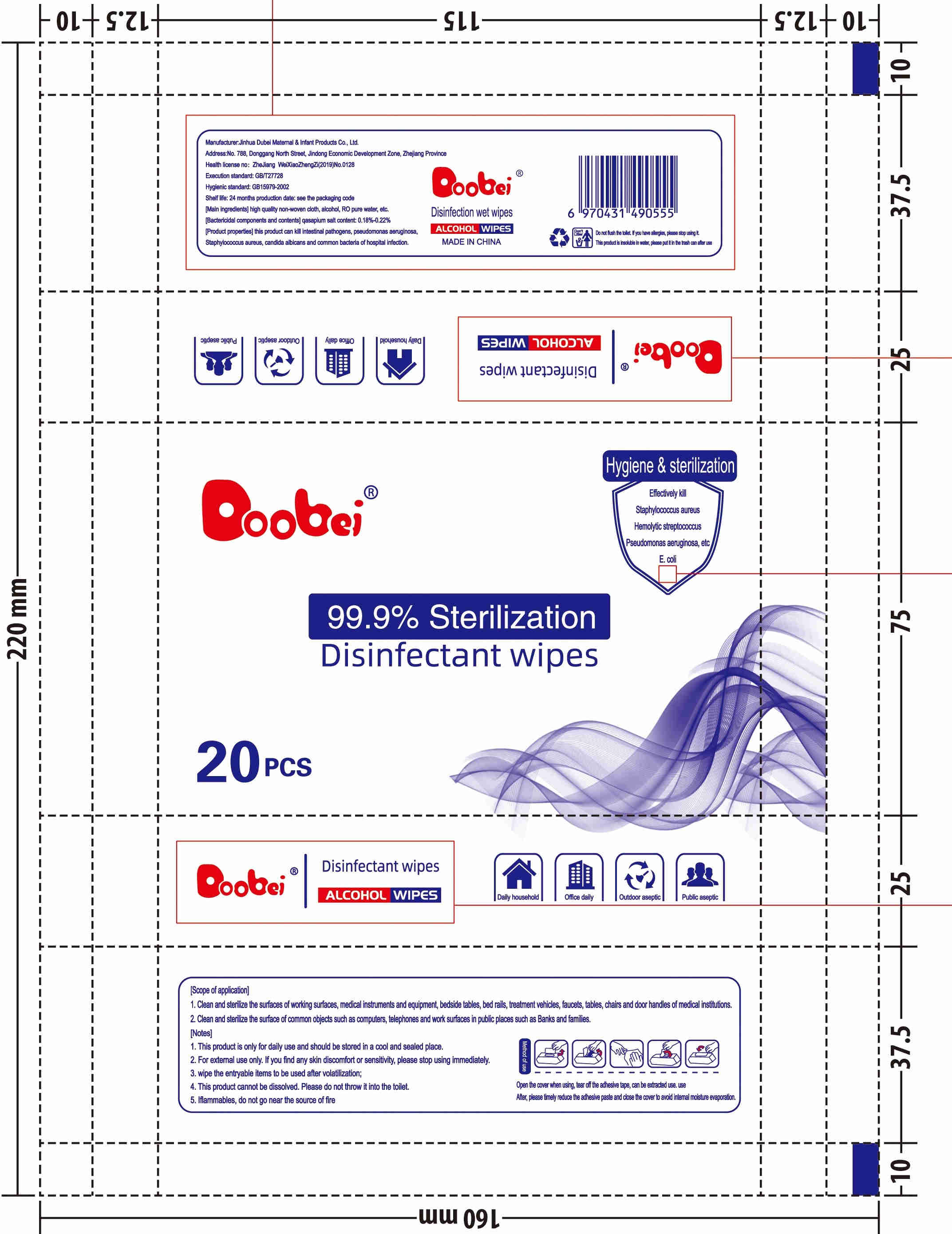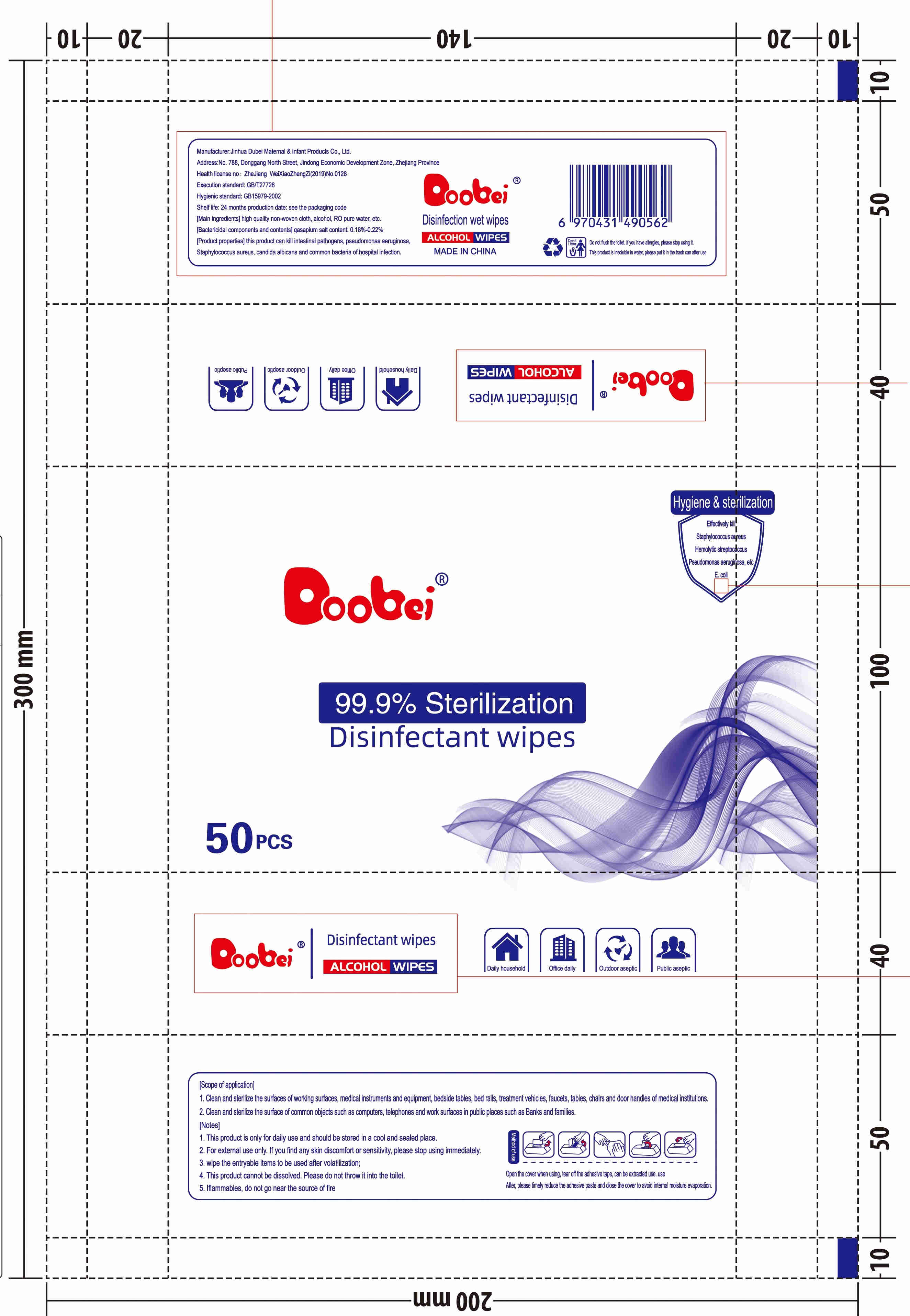 DRUG LABEL: DISINFECTANT WIPES
NDC: 41382-003 | Form: CLOTH
Manufacturer: Jinhua Dubei Maternal & Infant Products Co., Ltd.
Category: otc | Type: HUMAN OTC DRUG LABEL
Date: 20200521

ACTIVE INGREDIENTS: ALCOHOL 3.7 mL/10 1; BENZALKONIUM CHLORIDE 0.925 g/10 1
INACTIVE INGREDIENTS: WATER; 2-METHYL-4-ISOTHIAZOLIN-3-ONE HYDROCHLORIDE; DIDECYLDIMONIUM CHLORIDE; PHENOXYETHANOL; PROPYLENE GLYCOL

DOSAGE AND ADMINISTRATION

stored in a cool and sealed place.

INDICATIONS AND USAGE

Open the cover whenusing, tear of the adhesive tape, can be exracteduse. use Afer, please fimely reduce the adhesive paste and close the cover to avoid inemal moisure eaporation.

INACTIVE INGREDIENT

2-methyl-4-isothiazolin-3-one hydrochloride

2-phenoxyethanol

1,2-propanediol

water

Didecyl dimethyl ammonium chloride

ACTIVE INGREDIENT

Benzalkonium chloride

Alcohol

keep out of reach of children

PURPOSE

Disinfection
Sterilization
No Rinseing

WARNINGS

1. This product is only for daily use and should be stored in a cool and sealed place.
2. For extemal use only. If you find any skin discomfort or sensitivity, please stop using immediately.
3. wipe the entryable items to be used after vlatilization;
4. This product cannot be dissolved. Please do not throw it into the toilt.
5. Iflammables, do not go near the source of fire.